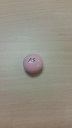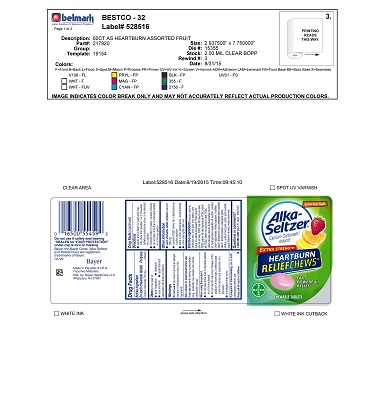 DRUG LABEL: Assorted Fruit Panned
NDC: 52642-228 | Form: TABLET, CHEWABLE
Manufacturer: BestCo
Category: otc | Type: HUMAN OTC DRUG LABEL
Date: 20160215

ACTIVE INGREDIENTS: CALCIUM CARBONATE 750 mg/1 1
INACTIVE INGREDIENTS: CARNAUBA WAX

Calcium Carbonate 750mg

ACTIVE INGREDIENT

Calcium Carbonate 750mg

Purpose

Antacid

INDICATIONS AND USAGE

Uses for the relief of:

- acid indigestion
- heartburn
- sour stomach
- upset stomach associated with these symptoms

Warnings

Do not use if you have ever had an allergic reaction to this product or any of its ingredients

Ask a doctor or pharmacist before use if you are presently taking a prescription drug. Antacids may interact with certain prescription drugs.

When using this product

- do not take more than 5 chewable tablets in a 24-hour period
- do not use the maximum dosage of this product for more than 2 weeks except under the adivce and supervision of a physician.
- constipation may occur

PREGNANCY OR BREAST FEEDING

If pregnant or breast-feeding, ask a health professional before use.

Keep out of reach of children.

Directions

- adults and children 12 years and over: fully chew then swallow 1 or 2 chewable tablets as symptoms occur, or as directed by a doctor.
- children under 12 years: consult a doctor
- do not take more than 5 chewable tablets in a 24-hour period

Other information

- each chewable tablet contains: calcium 300 mg
- contains FD&C Yellow No.5 (tartrazine) as a color additive
- store at room temperature. Avoid humiditity.
- close cap tightly after use.

Inactive Ingredients

acacia, carmine, carnauba wax, citric acid, corn starch, corn syrup, DL-alpha tocopherol, FD&C blue #1 aluminum lake, FD&C red #40 aluminum lake, FD&C yellow #5 (tartrazine), FD&C yellow #6 aluminum lake, FD&C yellow #6 lake, flavors, hydrogenated coconut oil, hydrogenated vegetable oil, lecithin, medium chain triglycerides, methly paraben, modified starch, phosphoric acid, pregelatinized modified starch, propyl paraben, propylene glycol, shellac, sodium benzoate, sorbic acid, sorbitol, sugar, titanium dioxide, water, white wax

Questions or comments?

1-800-986-0369 (Mon-Fri 9am-5pm EST)